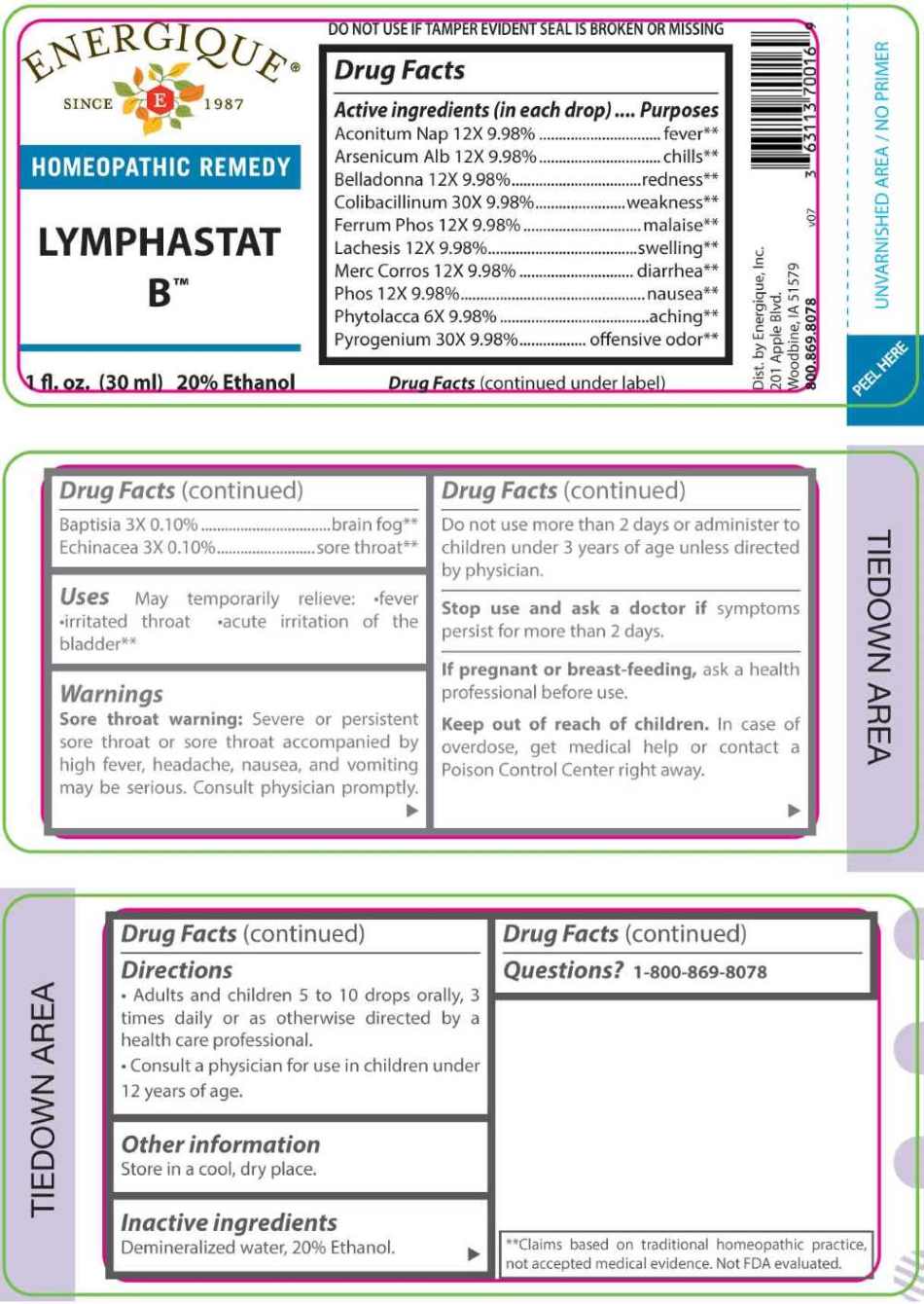 DRUG LABEL: Lymphastat B
NDC: 44911-0676 | Form: LIQUID
Manufacturer: Energique, Inc.
Category: homeopathic | Type: HUMAN OTC DRUG LABEL
Date: 20251124

ACTIVE INGREDIENTS: BAPTISIA TINCTORIA ROOT 3 [hp_X]/1 mL; ECHINACEA ANGUSTIFOLIA WHOLE 3 [hp_X]/1 mL; PHYTOLACCA AMERICANA ROOT 6 [hp_X]/1 mL; ACONITUM NAPELLUS WHOLE 12 [hp_X]/1 mL; ARSENIC TRIOXIDE 12 [hp_X]/1 mL; ATROPA BELLADONNA 12 [hp_X]/1 mL; FERROSOFERRIC PHOSPHATE 12 [hp_X]/1 mL; LACHESIS MUTA VENOM 12 [hp_X]/1 mL; MERCURIC CHLORIDE 12 [hp_X]/1 mL; PHOSPHORUS 12 [hp_X]/1 mL; ESCHERICHIA COLI 30 [hp_X]/1 mL; RANCID BEEF 30 [hp_X]/1 mL
INACTIVE INGREDIENTS: WATER; ALCOHOL

DRUG FACTS:

ACTIVE INGREDIENTS:

Aconitum Napellus 12X 9.98%, Arsenicum Album 12X 9.98%, Belladonna 12X 9.98%, Colibacillinum 30X 9.98%, Ferrum Phosphoricum 12X 9.98%, Lachesis Mutus 12X 9.98%, Mercurius Corrosivus 12X 9.98%, Phosphorus 12X 9.98%, Phytolacca Decandra 6X 9.98%, Pyrogenium 30X 9.98%, Baptisia Tinctoria 3X 0.10%, Echinacea 3X 0.10%.

PURPOSE:

Aconitum Napellus – fever**, Arsenicum Album – chills**, Belladonna – redness**, Colibacillinum – weakness**, Ferrum Phosphoricum – malaise**, Lachesis Mutus – swelling**, Mercurius Corrosivus – diarrhea**, Phosphorus – nausea**, Phytolacca Decandra – aching**, Pyrogenium – offensive odor**, Baptisia Tinctoria – brain fog**, Echinacea – sore throat**.

USES:

May temporarily relieve:

• fever • irritated throat

• acute irritation of the bladder**

**Claims based on traditional homeopathic practice, not accepted medical evidence. Not FDA evaluated.

WARNINGS:

Sore throat warning: Severe or persistent sore throat or sore throat accompanied by high fever, headache, nausea, and vomiting may be serious. Consult physician promptly. Do not use more than 2 days or administer to children under 3 years of age unless directed by a physician.

Stop use and ask a doctor if symptoms persist for more than 2 days.

If pregnant or breast-feeding, ask a health professional before use.

Keep out of reach of children. In case of overdose, get medical help or contact a Poison Control Center right away.

DO NOT USE IF TAMPER EVIDENT SEAL IS BROKEN OR MISSING

Store in a cool, dry place.

KEEP OUT OF REACH OF CHILDREN:

In case of overdose, get medical help or contact a Poison Control Center right away.

DIRECTIONS:

• Adults and children 5 to 10 drops orally, 3 times daily or as otherwise directed by a health care professional.

Consult a physician for use in children under 12 years of age.

INACTIVE INGREDIENTS:

Demineralized water, 20% Ethanol.

QUESTIONS:

Dist. by Energique, Inc.

201 Apple Blvd.

Woodbine, IA 51579

800.869.8078

PACKAGE LABEL DISPLAY:

ENERGIQUE

SINCE 1987

HOMEOPATHIC REMEDY

LYMPHASTAT B™

1 fl. oz. (30 ml)